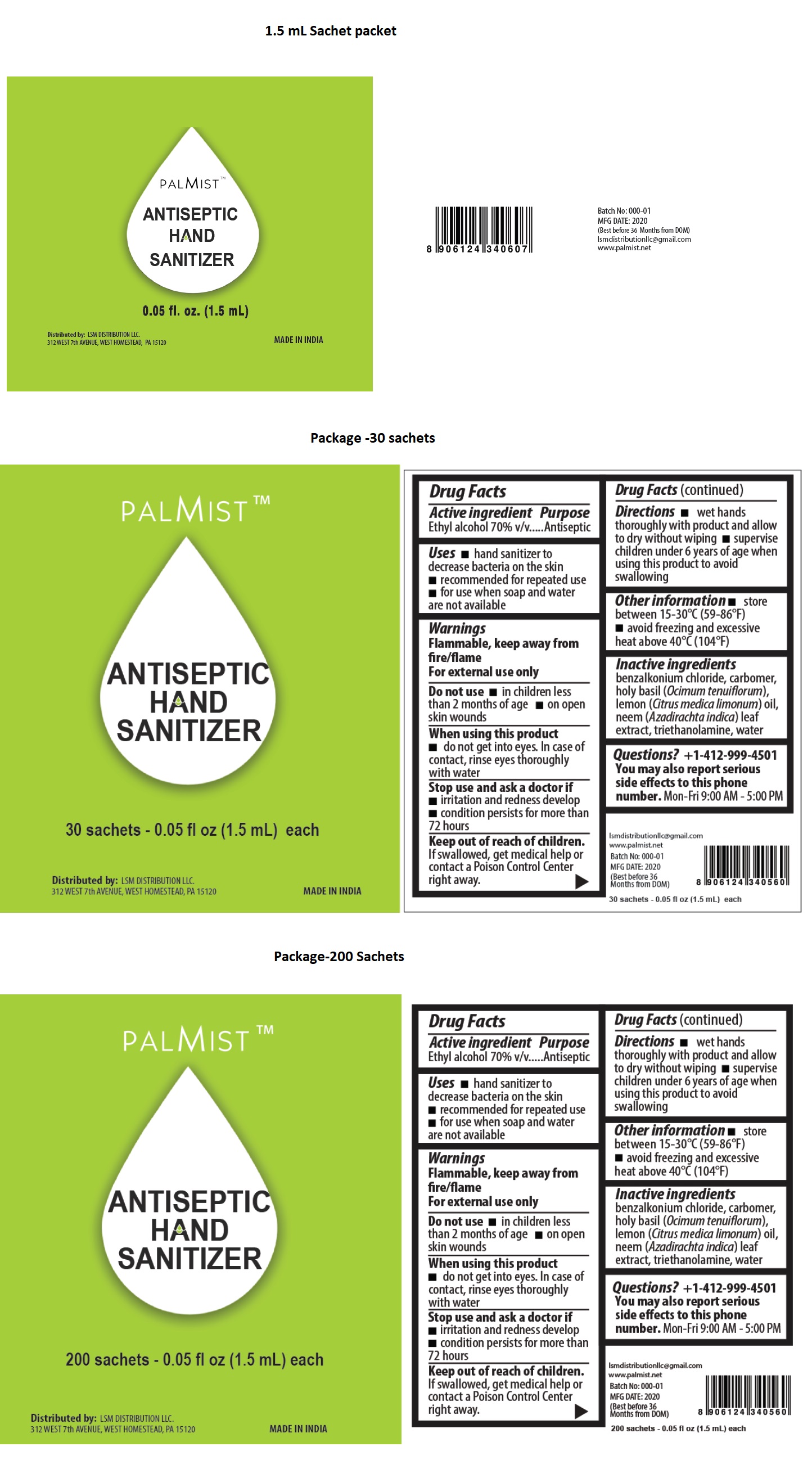 DRUG LABEL: PALMIST ANTISEPTIC HAND SANITIZER
NDC: 80636-101 | Form: GEL
Manufacturer: POCKET INC
Category: otc | Type: HUMAN OTC DRUG LABEL
Date: 20201027

ACTIVE INGREDIENTS: ALCOHOL 70 mL/100 mL
INACTIVE INGREDIENTS: BENZALKONIUM CHLORIDE; CARBOMER HOMOPOLYMER, UNSPECIFIED TYPE; HOLY BASIL LEAF; LEMON OIL; AZADIRACHTA INDICA LEAF; TROLAMINE; WATER

PALMISTTMANTISEPTIC HAND SANITIZER

Active ingredient

Ethyl alcohol 70% v/v

Purpose

Antiseptic

Uses

• hand sanitizer to decrease bacteria on the skin • recommended for repeated use • for use when soap and water are not available

Warnings

Flammable, keep away from fire/flame
For external use only

Do not use • in children less than 2 months of age • on open skin wounds

When using this product • do not get into eyes. In case of contact, rinse eyes thoroughly with water

Stop use and ask a doctor if • irritation and redness develop • condition persists for more than 72 hours

Keep out of reach of children. If swallowed, get medical help or contact a Poison Control Center right away.

Directions

• wet hands thoroughly with product and allow to dry without wiping • supervise children under 6 years of age when using this product to avoid swallowing

Other information

• store between 15-30°C (59-86°F) • avoid freezing and excessive heat above 40°C (104°F)

Inactive ingredients

benzalkonium chloride, carbomer, holy basil (Ocimum tenuiflorum), lemon (Citrus medica limonum) oil, neem (Azadirachta indica) leaf extract, triethanolamine, water

Questions?

+1-412-999-4501

You may also report serious side effects to this phone number. Mon-Fri 9:00 AM - 5:00 PM

Distributed by: LSM DISTRIBUTION LLC.
312 WEST 7th AVENUE, WEST HOMESTEAD, PA 15120

MADE IN INDIA

Ismdistributionllc@gmail.com

www.palmist.net